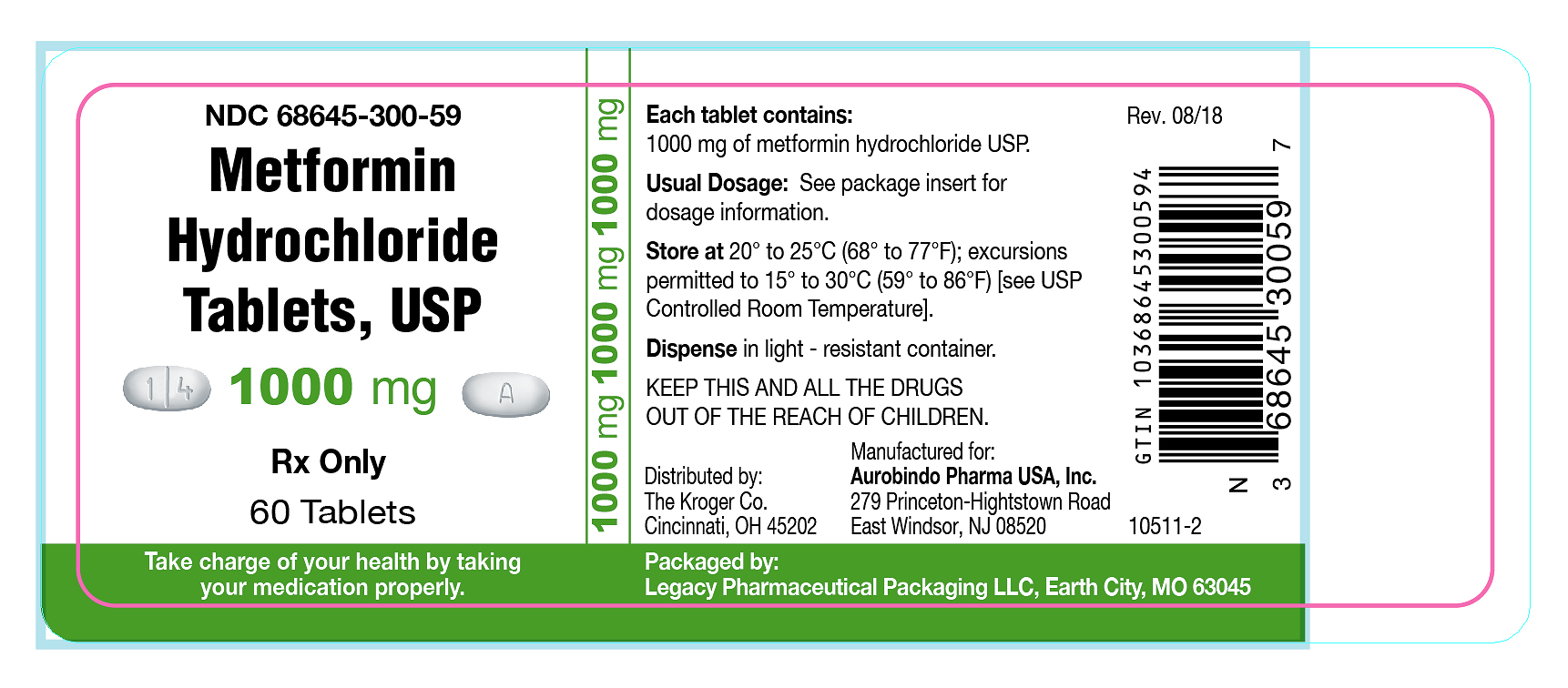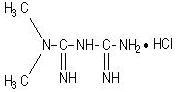 DRUG LABEL: Metformin Hydrochloride
NDC: 68645-300 | Form: TABLET, FILM COATED
Manufacturer: Legacy Pharmaceutical Packaging, LLC
Category: prescription | Type: HUMAN PRESCRIPTION DRUG LABEL
Date: 20251231

ACTIVE INGREDIENTS: METFORMIN HYDROCHLORIDE 1000 mg/1 1
INACTIVE INGREDIENTS: POLYETHYLENE GLYCOL 6000; POVIDONE K90; MAGNESIUM STEARATE; HYPROMELLOSE 2910 (5 MPA.S); POLYETHYLENE GLYCOL 400

Metformin Hydrochloride Tablets, USP

DESCRIPTION

Metformin hydrochloride tablets,USP are oral antihyperglycemic drugs used in the management of type 2 diabetes. Metformin hydrochloride (N,N-dimethylimidodicarbonimidic diamide hydrochloride) is not chemically or pharmacologically related to any other classes of oral antihyperglycemic agents. The structural formula is as shown:

Metformin hydrochloride, USP is a white to off-white crystalline compound with a molecular formula of C4H11N5• HCl and a molecular weight of 165.63. Metformin hydrochloride, USP is freely soluble in water and is practically insoluble in acetone, ether, and chloroform. The pKaof metformin is 12.4. The pH of a 1% aqueous solution of metformin hydrochloride is 6.68.
Metformin hydrochloride tablets, USP for oral administration, contains 500 mg, 850 mg, or 1000 mg of metformin hydrochloride USP. Each tablet contains the inactive ingredients povidone and magnesium stearate. In addition, the coating for the 500 mg, 850 mg, and 1000 mg contains hypromellose and polyethylene glycol.

CLINICAL PHARMACOLOGY

Mechanism of Action

Metformin is an antihyperglycemic agent which improves glucose tolerance in patients with type 2 diabetes, lowering both basal and postprandial plasma glucose. Its pharmacologic mechanisms of action are different from other classes of oral antihyperglycemic agents. Metformin decreases hepatic glucose production, decreases intestinal absorption of glucose, and improves insulin sensitivity by increasing peripheral glucose uptake and utilization. Unlike sulfonylureas, metformin does not produce hypoglycemia in either patients with type 2 diabetes or normal subjects (except in special circumstances, see PRECAUTIONS) and does not cause hyperinsulinemia. With metformin therapy, insulin secretion remains unchanged while fasting insulin levels and day-long plasma insulin response may actually decrease.

Pharmacokinetics

Absorption and Bioavailability

The absolute bioavailability of a metformin hydrochloride 500 mg tablet given under fasting conditions is approximately 50% to 60%. Studies using single oral doses of metformin hydrochloride tablets 500 to 1500 mg, and 850 to 2550 mg, indicate that there is a lack of dose proportionality with increasing doses, which is due to decreased absorption rather than an alteration in elimination. Food decreases the extent of and slightly delays the absorption of metformin, as shown by approximately a 40% lower mean peak plasma concentration (Cmax), a 25% lower area under the plasma concentration versus time curve (AUC), and a 35-minute prolongation of time to peak plasma concentration (Tmax) following administration of a single 850 mg tablet of metformin with food, compared to the same tablet strength administered fasting. The clinical relevance of these decreases is unknown.

Distribution

The apparent volume of distribution (V/F) of metformin following single oral doses of metformin hydrochloride tablets 850 mg averaged 654 ± 358 L. Metformin is negligibly bound to plasma proteins, in contrast to sulfonylureas, which are more than 90% protein bound. Metformin partitions into erythrocytes, most likely as a function of time. At usual clinical doses and dosing schedules of metformin hydrochloride tablets, steady state plasma concentrations of metformin are reached within 24 to 48 hours and are generally <1 mcg/mL. During controlled clinical trials of metformin hydrochloride tablets, maximum metformin plasma levels did not exceed 5 mcg/mL, even at maximum doses.

Metabolism and Elimination

Intravenous single-dose studies in normal subjects demonstrate that metformin is excreted unchanged in the urine and does not undergo hepatic metabolism (no metabolites have been identified in humans) nor biliary excretion. Renal clearance (see Table 1) is approximately 3.5 times greater than creatinine clearance, which indicates that tubular secretion is the major route of metformin elimination. Following oral administration, approximately 90% of the absorbed drug is eliminated via the renal route within the first 24 hours, with a plasma elimination half-life of approximately 6.2 hours. In blood, the elimination half-life is approximately 17.6 hours, suggesting that the erythrocyte mass may be a compartment of distribution.

Special Populations

Patients with Type 2 Diabetes

In the presence of normal renal function, there are no differences between single- or multiple-dose pharmacokinetics of metformin between patients with type 2 diabetes and normal subjects (see Table 1), nor is there any accumulation of metformin in either group at usual clinical doses.

Renal Impairment

In patients with decreased renal function, the plasma and blood half-life of metformin is prolonged and the renal clearance is decreased (see Table 1; also see CONTRAINDICATIONS, WARNINGS, PRECAUTIONS, and DOSAGE AND ADMINISTRATION).

Hepatic Impairment

No pharmacokinetic studies of metformin have been conducted in patients with hepatic insufficiency (see PRECAUTIONS).

Geriatrics

Limited data from controlled pharmacokinetic studies of metformin hydrochloride tablets in healthy elderly subjects suggest that total plasma clearance of metformin is decreased, the half-life is prolonged, and Cmaxis increased, compared to healthy young subjects. From these data, it appears that the change in metformin pharmacokinetics with aging is primarily accounted for by a change in renal function (see Table 1;also see WARNINGS, PRECAUTIONS,and DOSAGE AND ADMINISTRATION).

Table 1: Select Mean (±S.D.) Metformin Pharmacokinetic Parameters Following Single or Multiple Oral Doses of Metformin Hydrochloride Tablets
Subject Groups: Metformin Hydrochloride Tablets dosea(number of subjects) | Cmaxb(mcg/mL) | Tmaxc(hrs) | Renal Clearance (mL/min)
Healthy, nondiabetic adults: 500 mg single dose (24) 850 mg single dose (74)d 850 mg three times daily for 19 dosese(9) | 1.03 (±0.33) 1.6 (±0.38) 2.01 (±0.42) | 2.75 (±0.81) 2.64 (±0.82) 1.79 (±0.94) | 600 (±132) 552 (±139) 642 (±173)
Adults with type 2 diabetes: 850 mg single dose (23) 850 mg three times daily for 19 dosese(9) | 1.48 (±0.5) 1.9 (±0.62) | 3.32 (±1.08) 2.01 (±1.22) | 491 (±138) 550 (±160)
Elderlyf, healthy nondiabetic adults: 850 mg single dose (12) | 2.45 (±0.7) | 2.71 (±1.05) | 412 (±98)
Renal-impaired adults: 850 mg single dose Mild(CLcrg61 to 90 mL/min) (5) Moderate(CLcr31 to 60 mL/min) (4) Severe(CLcr10 to 30 mL/min) (6) | 1.86 (±0.52) 4.12 (±1.83) 3.93 (±0.92) | 3.2 (±0.45) 3.75 (±0.5) 4.01 (±1.1) | 384 (±122) 108 (±57) 130 (±90)
aAll doses given fasting except the first 18 doses of the multiple dose studies
bPeak plasma concentration
cTime to peak plasma concentration
dCombined results (average means) of five studies: mean age 32 years (range 23 to 59 years)
eKinetic study done following dose 19, given fasting
fElderly subjects, mean age 71 years (range 65 to 81 years)
gCLcr= creatinine clearance normalized to body surface area of 1.73 m^2

Pediatrics

After administration of a single oral metformin hydrochloride 500 mg tablet with food, geometric mean metformin Cmaxand AUC differed less than 5% between pediatric type 2 diabetic patients (12 to 16 years of age) and gender- and weight-matched healthy adults (20 to 45 years of age), all with normal renal function.

Gender

Metformin pharmacokinetic parameters did not differ significantly between normal subjects and patients with type 2 diabetes when analyzed according to gender (males = 19, females = 16). Similarly, in controlled clinical studies in patients with type 2 diabetes, the antihyperglycemic effect of metformin hydrochloride tablets was comparable in males and females.

Race

No studies of metformin pharmacokinetic parameters according to race have been performed. In controlled clinical studies of metformin hydrochloride tablets in patients with type 2 diabetes, the antihyperglycemic effect was comparable in whites (n=249), blacks (n=51), and Hispanics (n=24).

Clinical Studies

In a double-blind, placebo-controlled, multicenter U.S. clinical trial involving obese patients with type 2 diabetes whose hyperglycemia was not adequately controlled with dietary management alone (baseline fasting plasma glucose [FPG] of approximately 240 mg/dL), treatment with metformin hydrochloride tablets (up to 2550 mg/day) for 29 weeks resulted in significant mean net reductions in fasting and postprandial plasma glucose (PPG) and hemoglobin A1c(HbA1c) of 59 mg/dL, 83 mg/dL, and 1.8%, respectively, compared to the placebo group (see Table 2).

Table 2: Metformin Hydrochloride Tablets vs Placebo Summary of Mean Changes from Baseline* in Fasting Plasma Glucose, HbA1c, and Body Weight, at Final Visit (29-week study)
 | Metformin Hydrochloride Tablets (n = 141) | Placebo (n = 145) | p–Value
FPG (mg/dL) Baseline Change at FINAL VISIT | 241.5 -53 | 237.7 6.3 | NS** 0.001
Hemoglobin A1c(%) Baseline Change at FINAL VISIT | 8.4 -1.4 | 8.2 0.4 | NS** 0.001
Body Weight (lbs) Baseline Change at FINAL VISIT | 201 -1.4 | 206 -2.4 | NS ** NS **
*All patients on diet therapy at Baseline
**Not statistically significant

A 29-week, double-blind, placebo-controlled study of metformin hydrochloride tablets and glyburide, alone and in combination, was conducted in obese patients with type 2 diabetes who had failed to achieve adequate glycemic control while on maximum doses of glyburide (baseline FPG of approximately 250 mg/dL) (see Table 3). Patients randomized to the combination arm started therapy with metformin hydrochloride tablets 500 mg and glyburide 20 mg. At the end of each week of the first 4 weeks of the trial, these patients had their dosages of metformin hydrochloride tablets increased by 500 mg if they had failed to reach target fasting plasma glucose. After week 4, such dosage adjustments were made monthly, although no patient was allowed to exceed metformin hydrochloride tablets 2500 mg. Patients in the metformin hydrochloride tablets only arm (metformin plus placebo) followed the same titration schedule. At the end of the trial, approximately 70% of the patients in the combination group were taking metformin hydrochloride tablets 2000 mg/glyburide 20 mg or metformin hydrochloride tablets 2500 mg/glyburide 20 mg. Patients randomized to continue on glyburide experienced worsening of glycemic control, with mean increases in FPG, PPG, and HbA1cof 14 mg/dL, 3 mg/dL, and 0.2% respectively. In contrast, those randomized to metformin hydrochloride tablets (up to 2500 mg/day) experienced a slight improvement, with mean reductions in FPG, PPG, and HbA1cof 1 mg/dL, 6 mg/dL, and 0.4%, respectively. The combination of metformin hydrochloride tablets and glyburide was effective in reducing FPG, PPG, and HbA1clevels by 63 mg/dL, 65 mg/dL, and 1.7%, respectively. Compared to results of glyburide treatment alone, the net differences with combination treatment were -77 mg/dL, -68 mg/dL, and -1.9%, respectively (see Table 3).

Table 3: Combined Metformin Hydrochloride Tablets/Glyburide (Comb) vs Glyburide (Glyb) or Metformin Hydrochloride Tablets (MET) Monotherapy: Summary of Mean Changes from Baseline* in Fasting Plasma Glucose, HbA1c, and Body Weight, at Final Visit (29-week study)
 | Comb (n = 213) | Glyb (n = 209) | MET (n =210) | p-values
 | Glyb vs Comb | Glyb (n = 209) | MET (n =210) | MET vs Comb | MET vs Glyb
Fasting Plasma Glucose (mg/dL) Baseline Change at FINAL VISIT | 250.5 -63.5 | 247.5 13.7 | 253.9 -0.9 | NS** 0.001 | NS** 0.001 | NS** 0.025
Hemoglobin A1c(%) Baseline Change at FINAL VISIT | 8.8 -1.7 | 8.5 0.2 | 8.9 -0.4 | NS** 0.001 | NS** 0.001 | 0.007 0.001
Body Weight (lbs) Baseline Change at FINAL VISIT | 202.2 0.9 | 203 -0.7 | 204 -8.4 | NS** 0.011 | NS** 0.001 | NS** 0.001
* All patients on glyburide, 20 mg/day, at Baseline
** Not statistically significant

The magnitude of the decline in fasting blood glucose concentration following the institution of metformin hydrochloride tablets therapy was proportional to the level of fasting hyperglycemia. Patients with type 2 diabetes with higher fasting glucose concentrations experienced greater declines in plasma glucose and glycosylated hemoglobin.
In clinical studies, metformin hydrochloride tablets, alone or in combination with a sulfonylurea, lowered mean fasting serum triglycerides, total cholesterol, and LDL cholesterol levels, and had no adverse effects on other lipid levels (see Table 4).

Table 4: Summary of Mean Percent Change From Baseline of Major Serum Lipid Variables at Final Visit (29-week studies)
 | Metformin Hydrochloride Tablets vs Placebo | Combined Metformin Hydrochloride Tablets/Glyburide vs Monotherapy
 | Metformin Hydrochloride Tablets (n = 141) | Placebo (n = 145) | Metformin Hydrochloride Tablets (n = 210) | Metformin Hydrochloride Tablets/ Glyburide (n = 213) | Glyburide (n = 209)
Total Cholesterol (mg/dL) Baseline Mean % Change at FINAL VISIT | 211 -5% | 212.3 1% | 213.1 -2% | 215.6 -4% | 219.6 1%
Total Triglycerides (mg/dL) Baseline Mean % Change at FINAL VISIT | 236.1 -16% | 203.5 1% | 242.5 -3% | 215 -8% | 266.1 4%
LDL-Cholesterol (mg/dL) Baseline Mean % Change at FINAL VISIT | 135.4 -8% | 138.5 1% | 134.3 -4% | 136 -6% | 137.5 3%
HDL Cholesterol (mg/dL) Baseline Mean % Change at FINAL VISIT | 39 2% | 40.5 -1% | 37.2 5% | 39 3% | 37 1%

In contrast to sulfonylureas, body weight of individuals on metformin hydrochloride tablets tended to remain stable or even decrease somewhat (see Tables 2and 3).
A 24-week, double-blind, placebo-controlled study of metformin hydrochloride tablets plus insulin versus insulin plus placebo was conducted in patients with type 2 diabetes who failed to achieve adequate glycemic control on insulin alone (see Table 5). Patients randomized to receive metformin hydrochloride tablets plus insulin achieved a reduction in HbA1cof 2.1%, compared to a 1.56% reduction in HbA1cachieved by insulin plus placebo. The improvement in glycemic control was achieved at the final study visit with 16% less insulin, 93 U/day vs 110.6 U/day, metformin hydrochloride tablets plus insulin versus insulin plus placebo, respectively, p=0.04.

Table 5: Combined Metformin Hydrochloride Tablets/Insulin vs Placebo/Insulin Summary of Mean Changes from Baseline in HbA1cand Daily Insulin Dose
 | Metformin Hydrochloride Tablets/Insulin (n=26) | Placebo/ Insulin (n=28) | Treatment Difference Mean ± SE
Hemoglobin A1c(%) Baseline Change at FINAL VISIT | 8.95 -2.1 | 9.32 -1.56 | -0.54 ± 0.43a
Insulin Dose (U/day) Baseline Change at FINAL VISIT | 93.12 -0.15 | 94.64 15.93 | -16.08 ± 7.77b
aStatistically significant using analysis of covariance with baseline as covariate (p=0.04)
Not significant using analysis of variance (values shown in table)
bStatistically significant for insulin (p=0.04)

A second double-blind, placebo-controlled study (n=51), with 16 weeks of randomized treatment, demonstrated that in patients with type 2 diabetes controlled on insulin for 8 weeks with an average HbA1cof 7.46 ± 0.97%, the addition of metformin hydrochloride tablets maintained similar glycemic control (HbA1c7.15 ± 0.61 vs 6.97 ± 0.62 for metformin hydrochloride tablets plus insulin and placebo plus insulin, respectively) with 19% less insulin versus baseline (reduction of 23.68 ± 30.22 vs an increase of 0.43 ± 25.2 units for metformin hydrochloride tablets plus insulin and placebo plus insulin, p<0.01). In addition, this study demonstrated that the combination of metformin hydrochloride tablets plus insulin resulted in reduction in body weight of 3.11 ± 4.3 lbs, compared to an increase of 1.3 ± 6.08 lbs for placebo plus insulin, p=0.01.

Pediatric Clinical Studies

In a double-blind, placebo-controlled study in pediatric patients aged 10 to 16 years with type 2 diabetes (mean FPG 182.2 mg/dL), treatment with metformin hydrochloride tablets (up to 2000 mg/day) for up to 16 weeks (mean duration of treatment 11 weeks) resulted in significant mean net reduction in FPG of 64.3 mg/dL, compared with placebo (see Table 10).

Table 10: Metformin Hydrochloride Tablets vs Placebo (Pediatricsa) Summary of Mean Changes from Baseline* in Plasma Glucose and Body weight at Final Visit
 | Metformin Hydrochloride Tablets | Placebo | p-Value
FPG (mg/dL) Baseline Change at FINAL VISIT | (n=37) 162.4 -42.9 | (n=36) 192.3 21.4 | <0.001
Body Weight (lbs) Baseline Change at FINAL VISIT | (n=39) 205.3 -3.3 | (n=38) 189 -2 | NS**
aPediatric patients mean age 13.8 years (range 10 to 16 years)
* All patients on diet therapy at Baseline
** Not statistically significant

INDICATIONS AND USAGE

Metformin hydrochloride tablets are indicated as an adjunct to diet and exercise to improve glycemic control in adults and children with type 2 diabetes mellitus.

CONTRAINDICATIONS

Metformin hydrochloride tablets are contraindicated in patients with:

1. Severe renal impairment (eGFR below 30 mL/min/1.73 m) (see WARNINGSand PRECAUTIONS).
2. Known hypersensitivity to metformin hydrochloride.
3. Acute or chronic metabolic acidosis, including diabetic ketoacidosis, with or without coma. Diabetic ketoacidosis should be treated with insulin.

WARNINGS

Lactic Acidosis

Postmarketing cases of metformin-associated lactic acidosis have resulted in death, hypothermia, hypotension, and resistant bradyarrhythmias . The onset of metformin-associated lactic acidosis is often subtle, accompanied only by nonspecific symptoms such as malaise, myalgias , respiratory distress , somnolence, and abdominal pain. Metformin-associated lactic acidosis was characterized by elevated blood lactate levels (>5 mmol/Liter), anion gap acidosis (without evidence of ketonuria or ketonemia), an increased lactate/pyruvate ratio; and metformin plasma levels generally >5 mcg/mL (see PRECAUTIONS).

Risk factors for metformin-associated lactic acidosis include renal impairment, concomitant use of certain drugs (e.g. carbonic anhydrase inhibitors such as topiramate), age 65 years old or greater, having a radiological study with contrast, surgery and other procedures, hypoxic states (e.g., acute congestive heart failure), excessive alcohol intake, and hepatic impairment.

Steps to reduce the risk of and manage metformin-associated lactic acidosis in these high risk groups are provided (see DOSAGE AND ADMINISTRATION, CONTRAINDICATIONS, and PRECAUTIONS).

If metformin-associated lactic acidosis is suspected, immediately discontinue metformin hydrochloride tablets and institute general supportive measures in a hospital setting. Prompt hemodialysis is recommended (see PRECAUTIONS).

PRECAUTIONS

General

- Lactic acidosis— There have been postmarketing cases of metformin-associated lactic acidosis, including fatal cases. These cases had a subtle onset and were accompanied by nonspecific symptoms such as malaise, myalgias, abdominal pain, respiratory distress, or increased somnolence; however, hypotension and resistant bradyarrhythmias have occurred with severe acidosis. Metformin-associated lactic acidosis was characterized by elevated blood lactate concentrations (>5 mmol/L), anion gap acidosis (without evidence of ketonuria or ketonemia), and an increased lactate:pyruvate ratio; metformin plasma levels were generally >5 mcg/mL. Metformin decreases liver uptake of lactate increasing lactate blood levels which may increase the risk of lactic acidosis, especially in patients at risk.

If metformin-associated lactic acidosis is suspected, general supportive measures should be instituted promptly in a hospital setting, along with immediate discontinuation of metformin hydrochloride tablets. In metformin hydrochloride tablets treated patients with a diagnosis or strong suspicion of lactic acidosis, prompt hemodialysis is recommended to correct the acidosis and remove accumulated metformin (metformin hydrochloride is dialyzable with a clearance of up to 170 mL/min under good hemodynamic conditions). Hemodialysis has often resulted in reversal of symptoms and recovery.

Educate patients and their families about the symptoms of lactic acidosis and, if these symptoms occur, instruct them to discontinue metformin hydrochloride tablets and report these symptoms to their healthcare provider.

For each of the known and possible risk factors for metformin-associated lactic acidosis, recommendations to reduce the risk of and manage metformin-associated lactic acidosis are provided below:

- Renal impairment—The postmarketing metformin-associated lactic acidosis cases primarily occurred in patients with significant renal impairment.

The risk of metformin accumulation and metformin-associated lactic acidosis increases with the severity of renal impairment because metformin is substantially excreted by the kidney. Clinical recommendations based upon the patient’s renal function include (see DOSAGE AND ADMINISTRATION, CLINICAL PHARMACOLOGY):

- Before initiating metformin hydrochloride tablets, obtain an estimated glomerular filtration rate (eGFR)
- Metformin hydrochloride tablet is contraindicated in patients with an eGFR less than 30 mL/min/1.73 m^2(see CONTRAINDICATIONS).
- Initiation of metformin hydrochloride tablets are not recommended in patients with eGFR between 30 to 45 mL/min/1.73 m^2.
- Obtain an eGFR at least annually in all patients taking metformin hydrochloride tablets. In patients at risk for the development of renal impairment (e.g., the elderly), renal function should be assessed more frequently.
- In patients taking metformin hydrochloride tablets whose eGFR falls below 45 mL/min/1.73 m^2, assess the benefit and risk of continuing therapy.
- Drug interactions—The concomitant use of metformin hydrochloride tablets with specific drugs may increase the risk of metformin-associated lactic acidosis: those that impair renal function, result in significant hemodynamic change, interfere with acid-base balance, or increase metformin accumulation. Consider more frequent monitoring of patients.
- Age 65 or greater—The risk of metformin-associated lactic acidosis increases with the patient’s age because elderly patients have a greater likelihood of having hepatic, renal, or cardiac impairment than younger patients. Assess renal function more frequently in elderly patients.
- Radiologic studies with contrast—Administration of intravascular iodinated contrast agents in metformin-treated patients has led to an acute decrease in renal function and the occurrence of lactic acidosis. Stop metformin hydrochloride tablets at the time of, or prior to, an iodinated contrast imaging procedure in patients with an eGFR between 30 and 60 mL/min/1.73 m^2; in patients with a history of hepatic impairment, alcoholism or heart failure; or in patients who will be administered intra-arterial iodinated contrast. Re-evaluate eGFR 48 hours after the imaging procedure, and restart metformin hydrochloride tablets if renal function is stable.
- Surgery and other procedures—Withholding of food and fluids during surgical or other procedures may increase the risk for volume depletion, hypotension, and renal impairment. Metformin hydrochloride tablets should be temporarily discontinued while patients have restricted food and fluid intake.
- Hypoxic states—Several of the postmarketing cases of metformin-associated lactic acidosis occurred in the setting of acute congestive heart failure (particularly when accompanied by hypoperfusion and hypoxemia). Cardiovascular collapse (shock), acute myocardial infarction, sepsis, and other conditions associated with hypoxemia have been associated with lactic acidosis and may cause prerenal azotemia. When such an event occurs, discontinue metformin hydrochloride tablets.
- Excessivealcohol intake—Alcohol is known to potentiate the effect of metformin on lactate metabolism. Patients, therefore, should be warned against excessive alcohol intake, acute or chronic, while receiving metformin hydrochloride tablets.
- Hepatic impairment—Patients with hepatic impairment have developed cases of metformin-associated lactic acidosis. This may be due to impaired lactate clearance resulting in higher lactate blood levels. Therefore, avoid use of metformin hydrochloride tablets in patients with clinical or laboratory evidence of hepatic disease.

Vitamin B12levels —In controlled clinical trials of metformin hydrochloride tablets of 29 weeks duration, a decrease to subnormal levels of previously normal serum vitamin B12levels, without clinical manifestations, was observed in approximately 7% of patients. Such decrease, possibly due to interference with B12absorption from the B12-intrinsic factor complex, is, however, very rarely associated with anemia and appears to be rapidly reversible with discontinuation of metformin hydrochloride tablets or vitamin B12supplementation. Measurement of hematologic parameters on an annual basis is advised in patients on metformin and any apparent abnormalities should be appropriately investigated and managed (see PRECAUTIONS: Laboratory Tests).

Certain individuals (those with inadequate vitamin B12or calcium intake or absorption) appear to be predisposed to developing subnormal vitamin B12levels. In these patients, routine serum vitamin B measurements at 2- to 3-year intervals may be useful.

Hypoglycemia—Hypoglycemia does not occur in patients receiving metformin alone under usual circumstances of use, but could occur when caloric intake is deficient, when strenuous exercise is not compensated by caloric supplementation, or during concomitant use with other glucose-lowering agents (such as sulfonylureas and insulin) or ethanol.

Elderly, debilitated, or malnourished patients, and those with adrenal or pituitary insufficiency or alcohol intoxication are particularly susceptible to hypoglycemic effects. Hypoglycemia may be difficult to recognize in the elderly, and in people who are taking beta-adrenergic blocking drugs.

Macrovascular outcomes—There have been no clinical studies establishing conclusive evidence of macrovascular risk reduction with metformin hydrochloride tablets or any other antidiabetic drug.

Information for Patients

Patients should be informed of the potential risks and benefits of metformin and of alternative modes of therapy. They should also be informed about the importance of adherence to dietary instructions, of a regular exercise program, and of regular testing of blood glucose, glycosylated hemoglobin, renal function, and hematologic parameters.
The risks of lactic acidosis, its symptoms, and conditions that predispose to its development, as noted in the WARNINGSand PRECAUTIONSsections, should be explained to patients. Patients should be advised to discontinue metformin immediately and to promptly notify their health practitioner if unexplained hyperventilation, myalgia, malaise, unusual somnolence, or other nonspecific symptoms occur. Once a patient is stabilized on any dose level of metformin, gastrointestinal symptoms, which are common during initiation of metformin therapy, are unlikely to be drug related. Later occurrence of gastrointestinal symptoms could be due to lactic acidosis or other serious disease.
Patients should be counseled against excessive alcohol intake, either acute or chronic, while receiving metformin.
Metformin hydrochloride tablets alone does not usually cause hypoglycemia, although it may occur when metformin is used in conjunction with oral sulfonylureas and insulin. When initiating combination therapy, the risks of hypoglycemia, its symptoms and treatment, and conditions that predispose to its development should be explained to patients and responsible family members. (See Patient Informationprinted below.)

Laboratory Tests

Response to all diabetic therapies should be monitored by periodic measurements of fasting blood glucose and glycosylated hemoglobin levels, with a goal of decreasing these levels toward the normal range. During initial dose titration, fasting glucose can be used to determine the therapeutic response. Thereafter, both glucose and glycosylated hemoglobin should be monitored. Measurements of glycosylated hemoglobin may be especially useful for evaluating long-term control (see also DOSAGE AND ADMINISTRATION).
Initial and periodic monitoring of hematologic parameters (e.g., hemoglobin/hematocrit and red blood cell indices) and renal function (serum creatinine) should be performed, at least on an annual basis. While megaloblastic anemia has rarely been seen with metformin hydrochloride tablets therapy, if this is suspected, vitamin B12deficiency should be excluded.

Instruct patients to inform their doctor that they are taking metformin hydrochloride tablets prior to any surgical or radiological procedure, as temporary discontinuation of metformin hydrochloride tablets may be required until renal function has been confirmed to be normal (see PRECAUTIONS).

Drug Interactions (Clinical Evaluation of Drug Interactions Conducted with Metformin Hydrochloride Tablets)

Glyburide—In a single-dose interaction study in type 2 diabetes patients, coadministration of metformin and glyburide did not result in any changes in either metformin pharmacokinetics or pharmacodynamics. Decreases in glyburide AUC and Cmaxwere observed, but were highly variable. The single-dose nature of this study and the lack of correlation between glyburide blood levels and pharmacodynamic effects, makes the clinical significance of this interaction uncertain (see DOSAGE AND ADMINISTRATION: Concomitant Metformin and Oral Sulfonylurea Therapy in Adult Patients).
Furosemide— A single-dose, metformin-furosemide drug interaction study in healthy subjects demonstrated that pharmacokinetic parameters of both compounds were affected by coadministration. Furosemide increased the metformin plasma and blood Cmaxby 22% and blood AUC by 15%, without any significant change in metformin renal clearance. When administered with metformin, the Cmaxand AUC of furosemide were 31% and 12% smaller, respectively, than when administered alone, and the terminal half-life was decreased by 32%, without any significant change in furosemide renal clearance. No information is available about the interaction of metformin and furosemide when coadministered chronically.
Nifedipine— A single-dose, metformin-nifedipine drug interaction study in normal healthy volunteers demonstrated that coadministration of nifedipine increased plasma metformin Cmaxand AUC by 20% and 9%, respectively, and increased the amount excreted in the urine. Tmaxand half-life were unaffected. Nifedipine appears to enhance the absorption of metformin. Metformin had minimal effects on nifedipine.

Drugs that reduce metformin clearance—Concomitant use of drugs that interfere with common renal tubular transport systems involved in the renal elimination of metformin (e.g., organic cationic transporter-2 [OCT2]/multidrug and toxin extrusion [MATE] inhibitors such as ranolazine, vandetanib, dolutegravir, and cimetidine) could increase systemic exposure to metformin and may increase the risk for lactic acidosis. Consider the benefits and risks of concomitant use. Such interaction between metformin and oral cimetidine has been observed in normal healthy volunteers in both single-and multiple-dose, metformin-cimetidine drug interaction studies, with a 60% increase in peak metformin plasma and whole blood concentrations and a 40% increase in plasma and whole blood metformin AUC. There was no change in elimination half-life in the single-dose study. Metformin had no effect on cimetidine pharmacokinetics.
In healthy volunteers, the pharmacokinetics of metformin and propranolol, and metformin and ibuprofen were not affected when coadministered in single-dose interaction studies.

Metformin is negligibly bound to plasma proteins and is, therefore, less likely to interact with highly protein-bound drugs such as salicylates, sulfonamides, chloramphenicol, and probenecid, as compared to the sulfonylureas, which are extensively bound to serum proteins.

Other—Certain drugs tend to produce hyperglycemia and may lead to loss of glycemic control. These drugs include the thiazides and other diuretics, corticosteroids, phenothiazines, thyroid products, estrogens, oral contraceptives, phenytoin, nicotinic acid, sympathomimetics, calcium channel blocking drugs, and isoniazid. When such drugs are administered to a patient receiving metformin hydrochloride tablets, the patient should be closely observed for loss of blood glucose control. When such drugs are withdrawn from a patient receiving metformin hydrochloride tablets, the patient should be observed closely for hypoglycemia.

Carbonic anhydrase inhibitors—Topiramate or other carbonic anhydrase inhibitors (e.g., zonisamide, acetazolamide or dichlorphenamide) frequently cause a decrease in serum bicarbonate and induce nonunion gap, hyperchloremic metabolic acidosis. Concomitant use of these drugs with metformin hydrochloride tablets may increase the risk for lactic acidosis. Consider more frequent monitoring of these patients.

Alcohol—Alcohol is known to potentiate the effect of metformin on lactate metabolism. Warn patients against excessive alcohol intake while receiving metformin hydrochloride tablets.

Carcinogenesis, Mutagenesis, Impairment of Fertility

Long-term carcinogenicity studies have been performed in rats (dosing duration of 104 weeks) and mice (dosing duration of 91 weeks) at doses up to and including 900 mg/kg/day and 1500 mg/kg/day, respectively. These doses are both approximately 4 times the maximum recommended human daily dose of 2000 mg based on body surface area comparisons. No evidence of carcinogenicity with metformin was found in either male or female mice. Similarly, there was no tumorigenic potential observed with metformin in male rats. There was, however, an increased incidence of benign stromal uterine polyps in female rats treated with 900 mg/kg/day.
There was no evidence of a mutagenic potential of metformin in the following in vitrotests: Ames test (S. typhimurium), gene mutation test (mouse lymphoma cells), or chromosomal aberrations test (human lymphocytes). Results in the in vivomouse micronucleus test were also negative.
Fertility of male or female rats was unaffected by metformin when administered at doses as high as 600 mg/kg/day, which is approximately 3 times the maximum recommended human daily dose based on body surface area comparisons.

Pregnancy

Teratogenic effects

Pregnancy Category B
Recent information strongly suggests that abnormal blood glucose levels during pregnancy are associated with a higher incidence of congenital abnormalities. Most experts recommend that insulin be used during pregnancy to maintain blood glucose levels as close to normal as possible. Because animal reproduction studies are not always predictive of human response, metformin should not be used during pregnancy unless clearly needed.
There are no adequate and well-controlled studies in pregnant women with metformin. Metformin was not teratogenic in rats and rabbits at doses up to 600 mg/kg/day. This represents an exposure of about 2 and 6 times the maximum recommended human daily dose of 2000 mg based on body surface area comparisons for rats and rabbits, respectively. Determination of fetal concentrations demonstrated a partial placental barrier to metformin.

Nursing Mothers

Studies in lactating rats show that metformin is excreted into milk and reaches levels comparable to those in plasma. Similar studies have not been conducted in nursing mothers. Because the potential for hypoglycemia in nursing infants may exist, a decision should be made whether to discontinue nursing or to discontinue the drug, taking into account the importance of the drug to the mother. If metformin is discontinued, and if diet alone is inadequate for controlling blood glucose, insulin therapy should be considered.

Pediatric Use

The safety and effectiveness of metformin hydrochloride tablets for the treatment of type 2 diabetes have been established in pediatric patients ages 10 to 16 years (studies have not been conducted in pediatric patients below the age of 10 years). Use of metformin hydrochloride tablets in this age group is supported by evidence from adequate and well-controlled studies of metformin hydrochloride tablets in adults with additional data from a controlled clinical study in pediatric patients ages 10 to 16 years with type 2 diabetes, which demonstrated a similar response in glycemic control to that seen in adults. (See CLINICAL PHARMACOLOGY: Pediatric Clinical Studies.) In this study, adverse effects were similar to those described in adults. (See ADVERSE REACTIONS: Pediatric Patients.) A maximum daily dose of 2000 mg is recommended (see DOSAGE AND ADMINISTRATION: Recommended Dosing Schedule: Pediatrics).

Geriatric Use

Controlled clinical studies of metformin did not include sufficient numbers of elderly patients to determine whether they respond differently from younger patients, although other reported clinical experience has not identified differences in responses between the elderly and younger patients.

In general, dose selection for an elderly patient should be cautious, usually starting at the low end of the dosing range, reflecting the greater frequency of decreased hepatic, renal, or cardiac function, and of concomitant disease or other drug therapy and the higher risk of lactic acidosis. Assess renal function more frequently in elderly patients (see WARNINGS, PRECAUTIONS,and DOSAGE AND ADMINISTRATION).

ADVERSE REACTIONS

In a U.S. double-blind clinical study of metformin hydrochloride tablets in patients with type 2 diabetes, a total of 141 patients received metformin hydrochloride tablets therapy (up to 2550 mg per day) and 145 patients received placebo. Adverse reactions reported in greater than 5% of the metformin hydrochloride tablets patients, and that were more common in metformin hydrochloride tablets- than placebo-treated patients, are listed in Table 11.

Table 11: Most Common Adverse Reactions (>5 Percent) in a Placebo-Controlled Clinical Study of Metformin Hydrochloride Tablets Monotherapy*
Adverse Reaction | Metformin Hydrochloride Tablets Monotherapy (n = 141) | Placebo (n = 145)
Adverse Reaction | % of Patients
Diarrhea | 53.2 | 11.7
Nausea/Vomiting | 25.5 | 8.3
Flatulence | 12.1 | 5.5
Asthenia | 9.2 | 5.5
Indigestion | 7.1 | 4.1
Abdominal Discomfort | 6.4 | 4.8
Headache | 5.7 | 4.8
* Reactions that were more common in metformin hydrochloride tablets- than placebo-treated patients.

Diarrhea led to discontinuation of study medication in 6% of patients treated with metformin hydrochloride tablets. Additionally, the following adverse reactions were reported in ≥ 1% to ≤ 5% of metformin hydrochloride tablets patients and were more commonly reported with metformin hydrochloride tablets than placebo: abnormal stools, hypoglycemia, myalgia, lightheaded, dyspnea, nail disorder, rash, sweating increased, taste disorder, chest discomfort, chills, flu syndrome, flushing, palpitation.

Cholestatic, hepatocellular, and mixed hepatocellular liver injury have been reported with postmarketing use of metformin.

Pediatric Patients

In clinical trials with metformin hydrochloride tablets in pediatric patients with type 2 diabetes, the profile of adverse reactions was similar to that observed in adults.

OVERDOSAGE

Overdose of metformin hydrochloride has occurred, including ingestion of amounts greater than 50 grams. Hypoglycemia was reported in approximately 10% of cases, but no causal association with metformin hydrochloride has been established. Lactic acidosis has been reported in approximately 32% of metformin overdose cases (see WARNINGS). Metformin is dialyzable with a clearance of up to 170 mL/min under good hemodynamic conditions. Therefore, hemodialysis may be useful for removal of accumulated drug from patients in whom metformin overdosage is suspected.

DOSAGE AND ADMINISTRATION

There is no fixed dosage regimen for the management of hyperglycemia in patients with type 2 diabetes with metformin or any other pharmacologic agent. Dosage of metformin must be individualized on the basis of both effectiveness and tolerance, while not exceeding the maximum recommended daily doses. The maximum recommended daily dose of metformin hydrochloride tablets is 2550 mg in adults and 2000 mg in pediatric patients (10 to 16 years of age).
Metformin hydrochloride tablets should be given in divided doses with meals and should be started at a low dose, with gradual dose escalation, to reduce gastrointestinal side effects and to permit identification of the minimum dose required for adequate glycemic control of the patient.
During treatment initiation and dose titration (see Recommended Dosing Schedule), fasting plasma glucose should be used to determine the therapeutic response to metformin and identify the minimum effective dose for the patient. Thereafter, glycosylated hemoglobin should be measured at intervals of approximately 3 months. The therapeutic goal should be to decrease both fasting plasma glucose and glycosylated hemoglobin levels to normal or near normal by using the lowest effective dose of metformin, either when used as monotherapy or in combination with sulfonylurea or insulin.
Monitoring of blood glucose and glycosylated hemoglobin will also permit detection of primary failure, i.e., inadequate lowering of blood glucose at the maximum recommended dose of medication, and secondary failure, i.e., loss of an adequate blood glucose lowering response after an initial period of effectiveness.
Short-term administration of metformin may be sufficient during periods of transient loss of control in patients usually well-controlled on diet alone.

Recommended Dosing Schedule

Adults

The usual starting dose of metformin hydrochloride tablets is 500 mg twice a day or 850 mg once a day, given with meals. In general, clinically significant responses are not seen at doses below 1500 mg per day. Dosage increases should be made in increments of 500 mg weekly or 850 mg every 2 weeks, up to a total of 2000 mg per day, given in divided doses. The dosage of metformin hydrochloride tablets must be individualized on the basis of both effectiveness and tolerability. Patients can also be titrated from 500 mg twice a day to 850 mg twice a day after 2 weeks. For those patients requiring additional glycemic control, metformin hydrochloride tablets may be given to a maximum daily dose of 2550 mg per day. Doses above 2000 mg may be better tolerated given 3 times a day with meals.
Pediatrics – The usual starting dose of metformin hydrochloride tablets is 500 mg twice a day, given with meals. Dosage increases should be made in increments of 500 mg weekly up to a maximum of 2000 mg per day, given in divided doses. The dosage of metformin hydrochloride tablets must be individualized on the basis of both effectiveness and tolerability.

Recommendations for Use in Renal Impairment

Assess renal function prior to initiation of metformin hydrochloride tablets and periodically thereafter.

Metformin hydrochloride tablet is contraindicated in patients with an estimated glomerular filtration rate (eGFR) below 30 mL/minute/1.73 m^2.

Initiation of metformin hydrochloride tablets in patients with an eGFR between 30 to 45 mL/minute/1.73 m^2is not recommended.

In patients taking metformin hydrochloride tablets whose eGFR later falls below 45 mL/min/1.73 m^2, assess the benefit risk of continuing therapy.

Discontinue metformin hydrochloride tablets if the patient’s eGFR later falls below 30 mL/minute/1.73 m^2(See WARNINGSand PRECAUTIONS).

Discontinuation for Iodinated Contrast Imaging Procedures

Discontinue metformin hydrochloride tablets at the time of, or prior to, an iodinated contrast imaging procedure in patients with an eGFR between 30 and 60 mL/min/1.73 m^2; in patients with a history of liver disease, alcoholism, or heart failure; or in patients who will be administered intra-arterial iodinated contrast. Re-evaluate eGFR 48 hours after the imaging procedure; restart metformin hydrochloride tablets if renal function is stable.

Concomitant Metformin and Oral Sulfonylurea Therapy in Adult Patients

If patients have not responded to 4 weeks of the maximum dose of metformin monotherapy, consideration should be given to gradual addition of an oral sulfonylurea while continuing metformin at the maximum dose, even if prior primary or secondary failure to a sulfonylurea has occurred. Clinical and pharmacokinetic drug-drug interaction data are currently available only for metformin plus glyburide (glibenclamide).
With concomitant metformin and sulfonylurea therapy, the desired control of blood glucose may be obtained by adjusting the dose of each drug. In a clinical trial of patients with type 2 diabetes and prior failure on glyburide, patients started on metformin hydrochloride tablets 500 mg and glyburide 20 mg were titrated to 1000/20 mg, 1500/20 mg, 2000/20 mg, or 2500/20 mg of metformin hydrochloride tablets and glyburide, respectively, to reach the goal of glycemic control as measured by FPG, HbA1cand plasma glucose response (see CLINICAL PHARMACOLOGY: Clinical Studies). However, attempts should be made to identify the minimum effective dose of each drug to achieve this goal. With concomitant metformin and sulfonylurea therapy, the risk of hypoglycemia associated with sulfonylurea therapy continues and may be increased. Appropriate precautions should be taken. (See Package Insert of the respective sulfonylurea.)
If patients have not satisfactorily responded to 1 to 3 months of concomitant therapy with the maximum dose of metformin and the maximum dose of an oral sulfonylurea, consider therapeutic alternatives including switching to insulin with or without metformin.

Concomitant Metformin and Insulin Therapy in Adult Patients

The current insulin dose should be continued upon initiation of metformin therapy. Metformin therapy should be initiated at 500 mg once daily in patients on insulin therapy. For patients not responding adequately, the dose of metformin should be increased by 500 mg after approximately 1 week and by 500 mg every week thereafter until adequate glycemic control is achieved. The maximum recommended daily dose is 2500 mg for metformin hydrochloride tablets. It is recommended that the insulin dose be decreased by 10% to 25% when fasting plasma glucose concentrations decrease to less than 120 mg/dL in patients receiving concomitant insulin and metformin. Further adjustment should be individualized based on glucose-lowering response.

Specific Patient Populations

Metformin is not recommended for use in pregnancy. Metformin hydrochloride tablets are not recommended in patients below the age of 10 years.
The initial and maintenance dosing of metformin should be conservative in patients with advanced age, due to the potential for decreased renal function in this population. Any dosage adjustment should be based on a careful assessment of renal function.

HOW SUPPLIED

Metformin hydrochloride tablets, USP are supplied as:
Metformin Hydrochloride Tablets USP, 1000 mg:White, biconvex, oval shaped film coated tablets with a score line in between ‘1’ and ‘4’ on one side and ‘A’ debossed on the other side.
Bottles of 60 NDC68645-300-59

Storage
Store at 20° to 25°C (68° to 77°F); excursions permitted to 15° to 30°C (59° to 86°F) [see USP Controlled Room Temperature].
Dispense in light-resistant containers.

Patient Information

Metformin Hydrochloride Tablets, USP

Rx only
Read this information carefully before you start taking this medicine and each time you refill your prescription. There may be new information. This information does not take the place of your doctor’s advice. Ask your doctor or pharmacist if you do not understand some of this information or if you want to know more about this medicine.

What is metformin?

Metformin is used to treat type 2 diabetes. This is also known as non-insulin-dependent diabetes mellitus. People with type 2 diabetes are not able to make enough insulin or respond normally to the insulin their bodies make. When this happens, sugar (glucose) builds up in the blood. This can lead to serious medical problems including kidney damage, amputations, and blindness. Diabetes is also closely linked to heart disease. The main goal of treating diabetes is to lower your blood sugar to a normal level.
High blood sugar can be lowered by diet and exercise, by a number of medicines taken by mouth, and by insulin shots. Before you take metformin, try to control your diabetes by exercise and weight loss. While you take your diabetes medicine, continue to exercise and follow the diet advised for your diabetes. No matter what your recommended diabetes management plan is, studies have shown that maintaining good blood sugar control can prevent or delay complications of diabetes, such as blindness.
Metformin help control your blood sugar in a number of ways. These include helping your body respond better to the insulin it makes naturally, decreasing the amount of sugar your liver makes, and decreasing the amount of sugar your intestines absorb. Metformin do not cause your body to make more insulin. Because of this, when taken alone, they rarely cause hypoglycemia (low blood sugar), and usually do not cause weight gain. However, when they are taken with a sulfonylurea or with insulin, hypoglycemia is more likely to occur, as is weight gain.
Tell your doctor if you are pregnant or plan to become pregnant. Metformin may not be right for you. Talk with your doctor about your choices. You should also discuss your choices with your doctor if you are nursing a child.

Can metformin hydrochloride tablets be used in children?

Metformin hydrochloride tablets have been shown to effectively lower glucose levels in children (ages 10 to 16 years) with type 2 diabetes. Metformin hydrochloride tablets have not been studied in children younger than 10 years old. Metformin hydrochloride tablets have not been studied in combination with other oral glucose-control medicines or insulin in children. If you have any questions about the use of metformin hydrochloride tablets in children, talk with your doctor or other healthcare provider.

How should I take metformin hydrochloride tablets?

Your doctor will tell you how much medicine to take and when to take it. You will probably start out with a low dose of the medicine. Your doctor may slowly increase your dose until your blood sugar is better controlled. You should take metformin with meals.

Your doctor may have you take other medicines along with metformin to control your blood sugar. These medicines may include insulin shots. Taking metformin hydrochloride tablets with insulin may help you better control your blood sugar while reducing the insulin dose.

Continue your exercise and diet program and test your blood sugar regularly while taking metformin. Your doctor will monitor your diabetes and may perform blood tests on you from time to time to make sure your kidneys and your liver are functioning normally. There is no evidence that metformin causes harm to the liver or kidneys.

Tell your doctor if you:

- have an illness that causes severe vomiting, diarrhea or fever, or if you drink a much lower amount of liquid than normal. These conditions can lead to severe dehydration (loss of water in your body). You may need to stop taking metformin for a short time.
- plan to have surgery or an x-ray procedure with injection of dye (contrast agent). You may need to stop taking metformin hydrochloride tablets for a short time.
- start to take other medicines or change how you take a medicine. Metformin can affect how well other drugs work, and some drugs can affect how well metformin work. Some medicines may cause high blood sugar.

What should I avoid while taking metformin hydrochloride tablets?

Do not drink a lot of alcoholic drinks while taking metformin. This means you should not binge drink for short periods, and you should not drink a lot of alcohol on a regular basis. Alcohol can increase the chance of getting lactic acidosis.

What are the side effects of metformin?

- Lactic acidosis . Metformin, the active ingredient in metformin hydrochloride tablets , can cause a rare but serious condition called lactic acidosis (a buildup of an acid in the blood) that can cause death. Lactic acidosis is a medical emergency and must be treated in the hospital.

Call your doctor right away if you have any of the following symptoms, which could be signs of lactic acidosis:

- you feel cold in your hands or feet
- you feel dizzy or lightheaded
- you have a slow or irregular heartbeat
- you feel very weak or tired
- you have unusual (not normal) muscle pain
- you have trouble breathing
- you feel sleepy or drowsy
- you have stomach pains, nausea or vomiting

Most people who have had lactic acidosis with metformin have other things that, combined with the metformin, led to the lactic acidosis. Tell your doctor if you have any of the following, because you have a higher chance for getting lactic acidosis with metformin if you:

- have severe kidney problems, or your kidneys are affected by certain x-ray tests that use injectable dye
- have liver problems
- drink alcohol very often, or drink a lot of alcohol in short-term "binge" drinking
- get dehydrated (lose a large amount of body fluids). This can happen if you are sick with a fever, vomiting, or diarrhea. Dehydration can also happen when you sweat a lot with activity or exercise and do not drink enough fluids
- have surgery
- have a heart attack, severe infection, or stroke

The best way to keep from having a problem with lactic acidosis from metformin is to tell your doctor if you have any of the problems in the list above. Your doctor may decide to stop your metformin hydrochloride tablets for a while if you have any of these things.

Other Side Effects. Common side effects of metformin include diarrhea, nausea, and upset stomach. These side effects generally go away after you take the medicine for a while. Taking your medicine with meals can help reduce these side effects. Tell your doctor if the side effects bother you a lot, last for more than a few weeks, come back after they’ve gone away, or start later in therapy. You may need a lower dose or need to stop taking the medicine for a short period or for good.

About 3 out of every 100 people who take metformin hydrochloride tablets have an unpleasant metallic taste when they start taking the medicine. It lasts for a short time.

Metformin hydrochloride tablets rarely cause hypoglycemia (low blood sugar) by themselves. However, hypoglycemia can happen if you do not eat enough, if you drink alcohol, or if you take other medicines to lower blood sugar .

General advice about prescription medicines

If you have questions or problems, talk with your doctor or other healthcare provider. You can ask your doctor or pharmacist for the information about metformin that is written for health care professionals. Medicines are sometimes prescribed for purposes other than those listed in a patient information leaflet. Do not use metformin for a condition for which it was not prescribed. Do not share your medicine with other people.
Manufactured for:
Aurobindo Pharma USA, Inc.
2400 Route 130 North
Dayton, NJ 08810
Manufactured by:
Aurobindo Pharma Limited
Unit-VII (SEZ)
Mahabubnagar (Dt)-509302
India

Distributed by:
The Kroger Co.
Cincinnati, OH 45202

Packaged by:
Legacy Pharmaceutical Packaging, LLC
Earth City, MO 63045
Revised: 07/2018